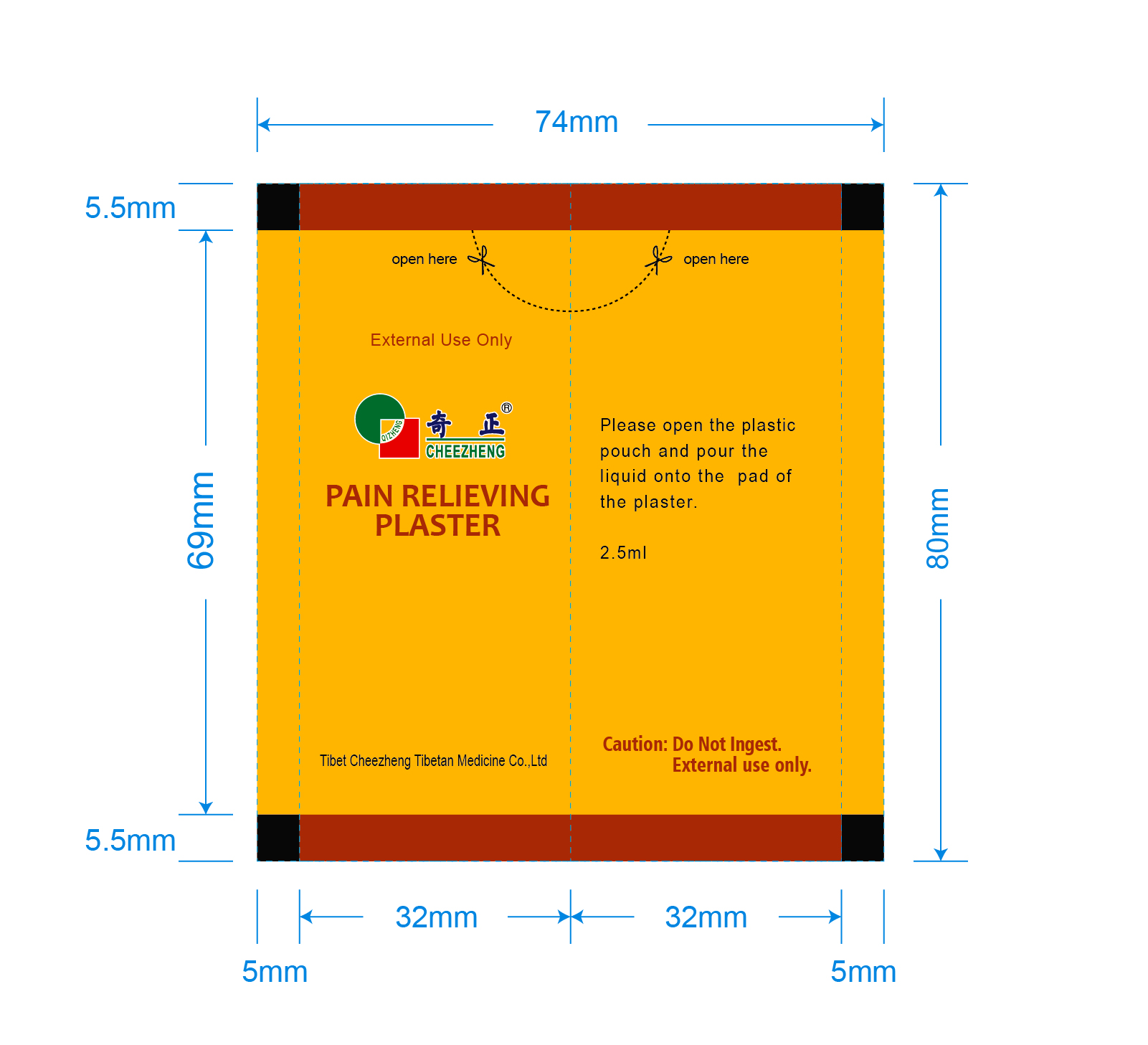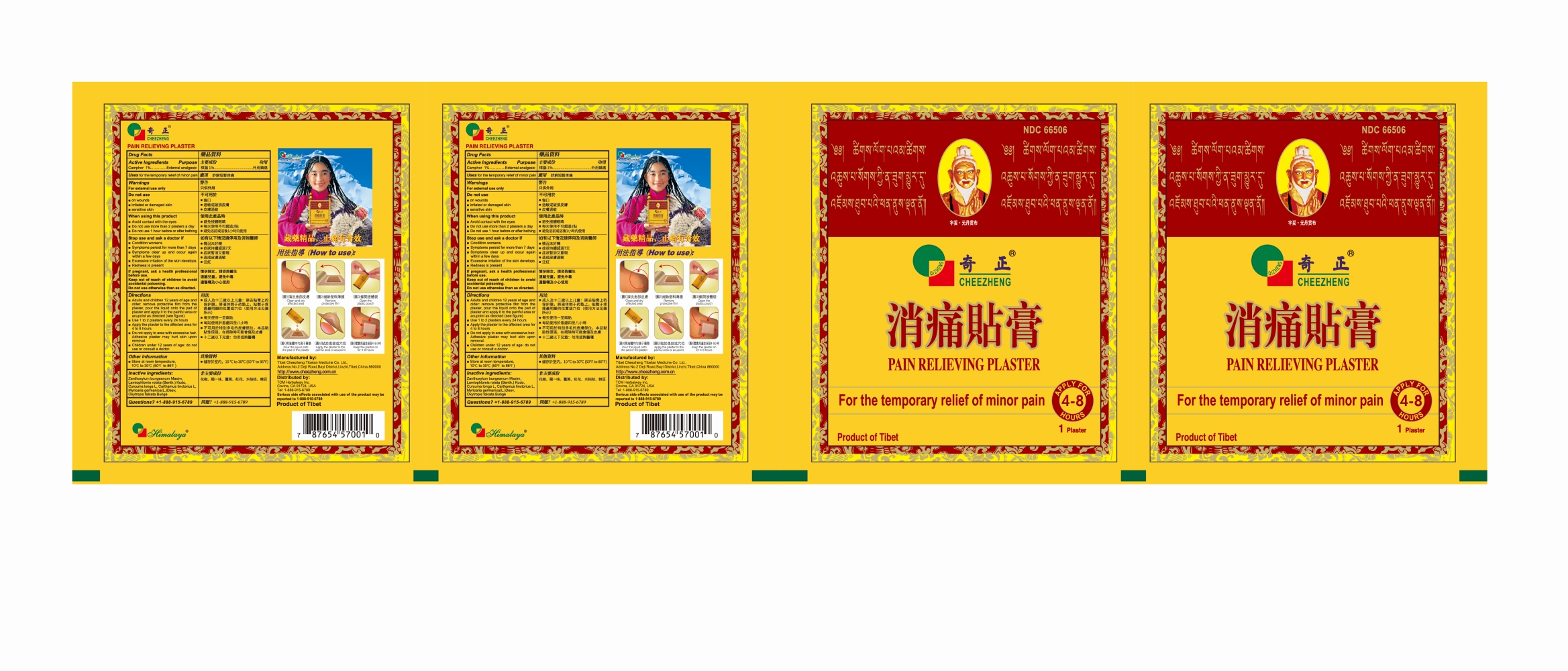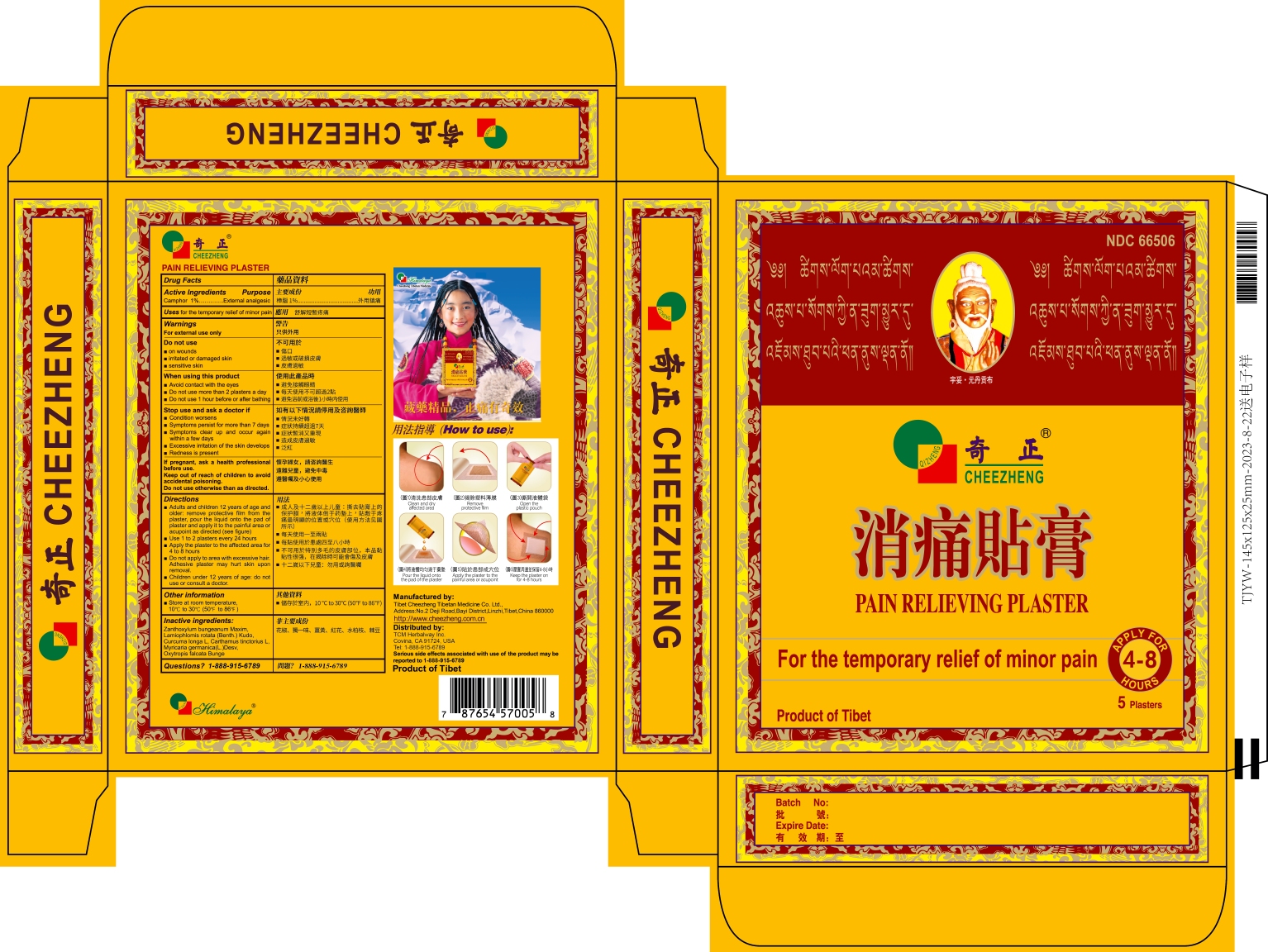 DRUG LABEL: CheeZheng Pain Relieveing Plaster
NDC: 66506-183 | Form: PLASTER
Manufacturer: Tibet Cheezheng Tibetan Medicine Co. Ltd.
Category: otc | Type: HUMAN OTC DRUG LABEL
Date: 20250211

ACTIVE INGREDIENTS: CAMPHOR (NATURAL) 1 g/100 g
INACTIVE INGREDIENTS: ZANTHOXYLUM BUNGEANUM FRUIT RIND; CURCUMA LONGA WHOLE; CARTHAMUS TINCTORIUS FLOWER BUD; PHLOMOIDES ROTATA WHOLE; MYRICARIA PANICULATA STEM; OXYTROPIS FALCATA WHOLE

CheeZheng Pain Relieveing Plaster

Active ingredients

Camphor 1%.................……….…….External analgesic

Do not use otherwise than as directed

Keep out of reach of children to avoid accidental poisoning

If pregnant

If pregnant, ask a health professional before use

Directions

■Adults and children 12 years of age and older: remove protective film from the plaster, pour the liquid onto the pad of plaster and apply it to the painful area or acupoint as directed (see figure)
■Use 1 to 2 plasters every 24 hours
■Apply the plaster to the affected area for 4 to 8 hours
■Do not apply to area with excessive hair. Adhesive plaster may hurt skin upon removal.
■Children under 12 years of age: do not use or consult a doctor.

Other information

Store at room temperature, 10 ℃ to 30℃ (50℉ to 86℉)

Inactive ingredients

Zanthoxylum bungeanum Maxim, Lamiophlomis rotata (Benth.) Kudo, Curcuma longa L, Carthamus tinctorius L, Myricaria germanica (L.) Desv, Oxytropis falcata Bunge

Questions?

+1-888-915-6789

Purpose

External analgesic

Do not use

- on wounds
- irritated or damaged skin
- sensitive skin

When using this product

- avoid contact with the eyes
- do not use more than 2 plasters a day
- do not use 1 hour before or after bathing

Stop use and ask a doctor if

- Condition worsens
- Symptoms persist for more than 7 days
- Symptoms clear up and occur again within a few days
- Eexcessive irritation of the skin develops
- Redness is present

Warnings

For external use only

Uses

For the temporary relief of minor pain.